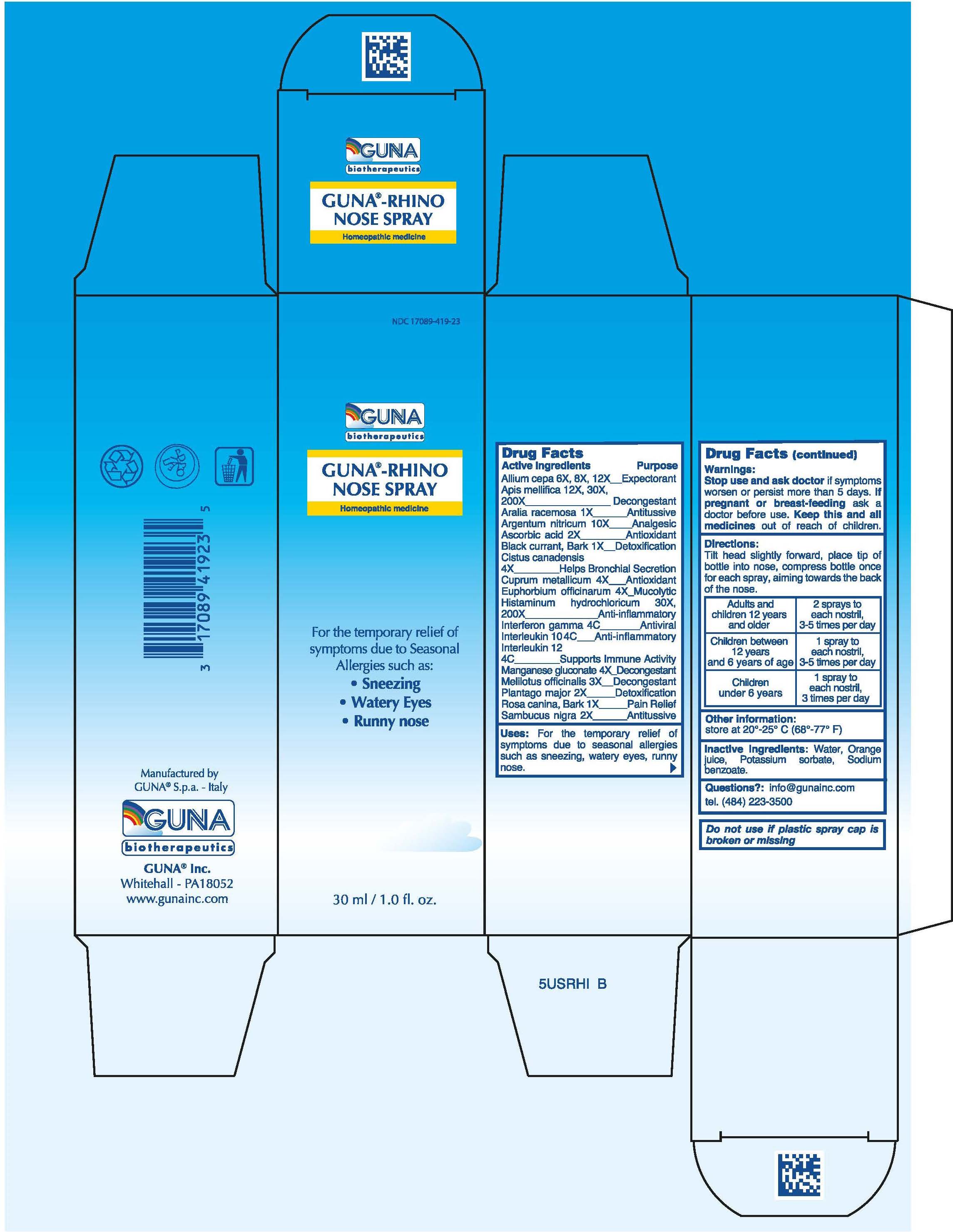 DRUG LABEL: GUNA-RHINO NOSE
NDC: 17089-419 | Form: SPRAY
Manufacturer: Guna spa
Category: homeopathic | Type: HUMAN OTC DRUG LABEL
Date: 20181221

ACTIVE INGREDIENTS: ONION 8 [hp_X]/30 mL; APIS MELLIFERA 12 [hp_X]/30 mL; ARALIA RACEMOSA ROOT 1 [hp_X]/30 mL; SILVER NITRATE 10 [hp_X]/30 mL; ASCORBIC ACID 2 [hp_X]/30 mL; BLACK CURRANT 1 [hp_X]/30 mL; HELIANTHEMUM CANADENSE 4 [hp_X]/30 mL; COPPER 4 [hp_X]/30 mL; EUPHORBIA RESINIFERA RESIN 4 [hp_X]/30 mL; HISTAMINE DIHYDROCHLORIDE 200 [hp_X]/30 mL; INTERFERON GAMMA-1B 4 [hp_C]/30 mL; INTERLEUKIN-10 4 [hp_C]/30 mL; HUMAN INTERLEUKIN 12 4 [hp_C]/30 mL; MANGANESE GLUCONATE 4 [hp_X]/30 mL; MELILOTUS 3 [hp_X]/30 mL; PLANTAGO MAJOR 2 [hp_X]/30 mL; ROSA CANINA FRUIT 1 [hp_X]/30 mL; EUROPEAN ELDERBERRY 2 [hp_X]/30 mL
INACTIVE INGREDIENTS: ORANGE JUICE 0.6 mL/30 mL; POTASSIUM SORBATE 0.03 mL/30 mL; WATER 15.9 mL/30 mL; SODIUM BENZOATE 0.03 mL/30 mL

guna-rhino nose spray

ACTIVE INGREDIENTS/PURPOSE

ALIUM CEPA 6X, 8X, 12X EXPECTORANT
APIS MELLIFICA 12x, 30X, 200X DECONGESTANT
ARALIA RACEMOSA 1X ANTITUSSIVE
ARGENTUM NITRICUM 10X ANALGESIC
ASCORBIC ACID 2X ANTIOXIDANT
BLACK CURRANT, BARK 1X DETOXIFICATION
CISTUS CANADENSIS 4X HELPS BRONCHIAL SECRETION
CUPRUM METALLICUM 4X ANTIOXIDANT
EUPHORBIUM OFFICINARUM 4X MUCOLYTIC
HISTAMINUM HYDROCHLORICUM 30X, 200X ANTI-INFLAMMATORY
INTERFERON GAMMA 4C ANTIVIRAL
INTERLEUKIN 10 4C ANTI-INFLAMMATORY
INTERLEUKIN 12 4C SUPPORTS IMMUNE ACTIVITY
MANGANESE GLUCONATE 4X DECONGESTANT
MELILOTUS OFFICINALIS 3X DECONGESTANT
PLANTAGO MAJOR 2X DETOXIFICATION
ROSA CANINA, BARK 1X PAIN RELIEF
SAMBUCUS NIGRA 2X ANTITUSSIVE

USES

For the temporary relief of symptoms due to Seasonal Allergies such as: Sneezing, Watery Eyes, Runny nose

WARNINGS

Stop use and ask doctor if symptoms worsen or persist more than 5 days

PREGNANCY

If pregnant or breast-feeding ask a doctor before use

WARNINGS

Keep this and all medicines out of reach of children

DIRECTIONS

Adults and children 12 years and older 2 sprays to each nostril , 3-5 times per day
Children between 12 years and 6 years of age 1 spray to each nostril, 3-5 times per day
Children under 6 years 1 spray to each nostril, 3 times per day

QUESTIONS

Questions?: info@gunainc.com
Tel. (484) 223-3500

INDICATIONS AND USAGE

Tilt head slightly forward, place tip of bottle into nose, compress bottle once for each spray, aiming towards the back of the nose.

INACTIVE INGREDIENT

Inactive ingredients: Water, Orange juice, Potassium sorbate, Sodium benzoate